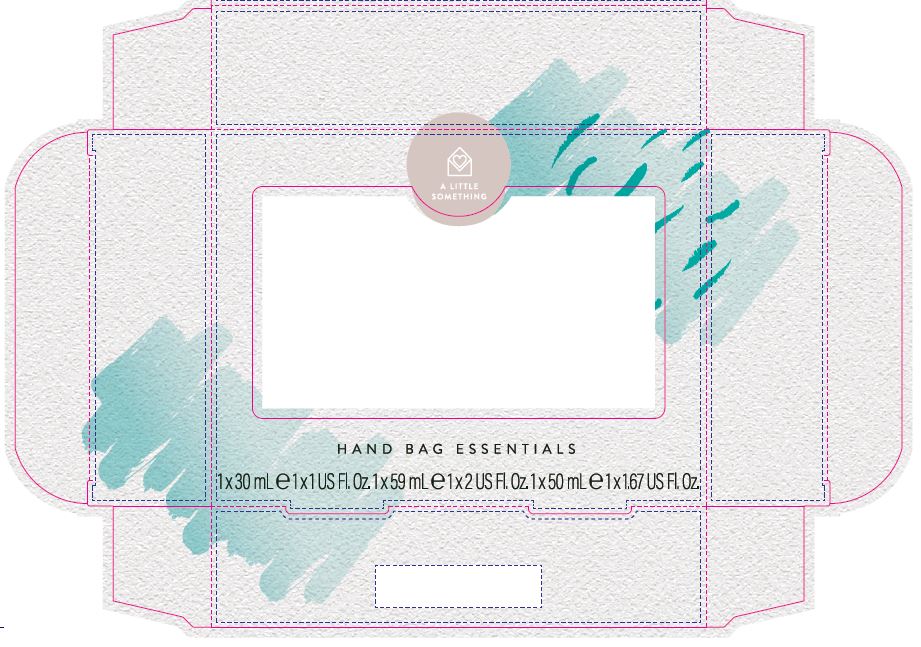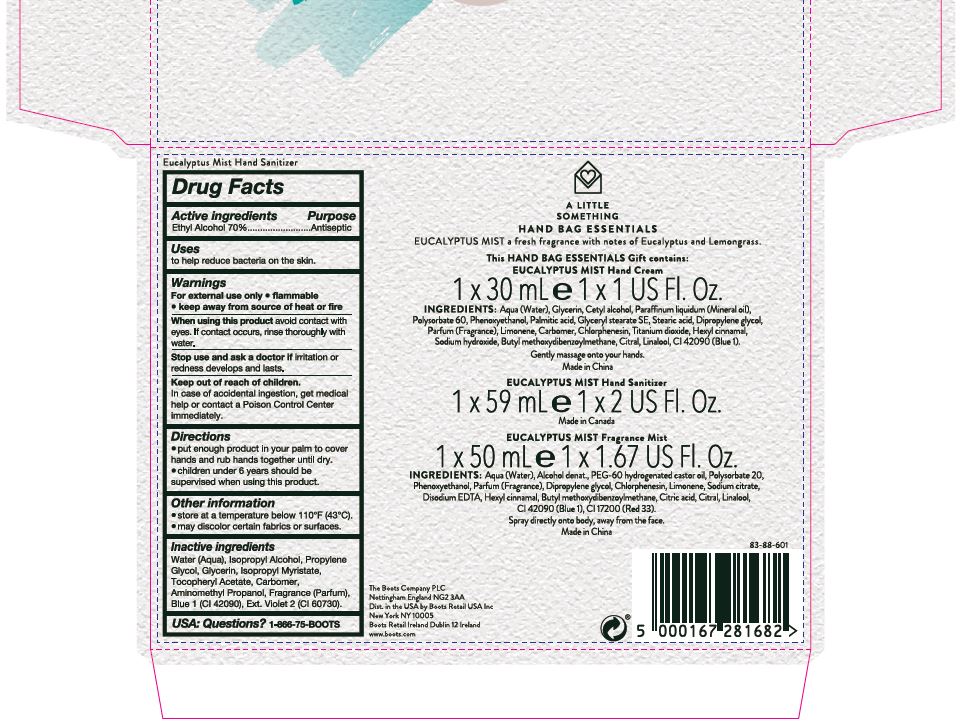 DRUG LABEL: A Little Something Eucalyptus Mist Hand Sanitier
NDC: 0363-1050 | Form: LIQUID
Manufacturer: Walgreen Company
Category: otc | Type: HUMAN OTC DRUG LABEL
Date: 20201217

ACTIVE INGREDIENTS: ALCOHOL 700 mg/1 mL
INACTIVE INGREDIENTS: WATER; ISOPROPYL ALCOHOL; PROPYLENE GLYCOL; GLYCERIN; ISOPROPYL MYRISTATE; .ALPHA.-TOCOPHEROL ACETATE, DL-; CARBOMER 934; AMINOMETHYLPROPANOL; FD&C BLUE NO. 1; EXT. D&C VIOLET NO. 2

A Little Something Hand Bag Essentials - Eucalyptus Mist

Active ingredients

Ethyl Alcohol 70%

Purpose

Pupose

Antiseptic

Uses

to help reduce bacteria on the skin.

Warnings

For external use only

flammable

keep away fro source of heat or fire

When using

When using this product avoid contact with eyes. If contact occurs, rinse thoroughly with water

Stop use

Stop use and ask a doctor if irritation or redness develops and lasts.

Keep out of reach of children

In case of accidental ingestion, get medical help or contact a Poison Control Center immediately.

Directions

put enough product in your palm to cover hands and rub hands together until dry.

children under 6 years should be supervised when using this product.

Other information

store at a temperature below 110F (43C).

may discolor certain fabrics or surfaces.

Inactive ingredients

Water (Aqua), Isopropyl Alcohol, Propylene Glycol, Glycerin, Isopropyl Myristate, Tocopheryl Acetate, Carbomer, Aminomethyl Propanol, Fragrance (Parfum), Blue 1 (CI 42090), Ext. Violet 2 (CI 60730).

Questions

USA: Questions? 1-866075-BOOTS

Description

A Little Something

Hand Bag Essentials

1 x 59 ml e 1 x 2 US Fl. Oz.

This Hand Bag Essentials Gift contains:

EUCALYPTUS MIST Hand Sanitizer

1 x 59 ml e 1 x 2 US Fl. Oz.

Made in Canada

The Boots Company PLC

Nottingham England NG2 3AA

Dist. in the USA by Boots Retail USA Inc

New York NY 10005

Boots Retail Ireland Dublin 12 Ireland

Carton